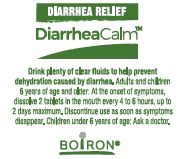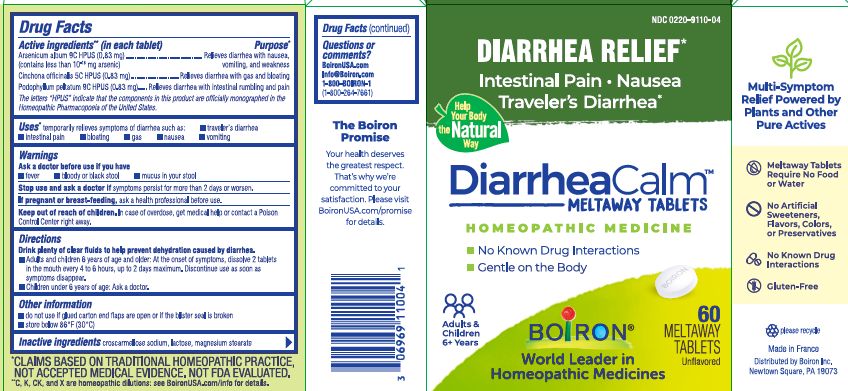 DRUG LABEL: DiarrheaCalm
NDC: 0220-9110 | Form: TABLET
Manufacturer: Boiron
Category: homeopathic | Type: HUMAN OTC DRUG LABEL
Date: 20250312

ACTIVE INGREDIENTS: CINCHONA OFFICINALIS BARK 5 [hp_C]/1 1; PODOPHYLLUM 9 [hp_C]/1 1; ARSENIC TRIOXIDE 9 [hp_C]/1 1
INACTIVE INGREDIENTS: CROSCARMELLOSE SODIUM; MAGNESIUM STEARATE; LACTOSE, UNSPECIFIED FORM

DiarrheaCalm tablets

Active ingredients** (in each tablet)

Arsenicum album 9C HPUS (0.83 mg) (contains less than 10^-18 mg arsenic)

Cinchona officinalis 5C HPUS (0.83 mg)

Podophyllum peltatum 9C HPUS (0.83 mg)

The letters “HPUS” indicate that the components in this product are officially monographed in the Homeopathic Pharmacopoeia of the United States.

Uses*

temporarily relieves symptoms of diarrhea such as:

▪ traveler’s diarrhea ▪ intestinal pain ▪ bloating ▪ gas ▪ nausea ▪ vomiting

Purpose*

Arsenicum album 9C HPUS (0.83 mg)………. Relieves diarrhea with nausea, vomiting, and weakness

Cinchona officinalis 5C HPUS (0.83 mg)……..………Relieves diarrhea with gas and bloating

Podophyllum peltatum 9C HPUS (0.83 mg)……Relieves diarrhea with intestinal rumbling and pain

Ask a doctor before use if you have

▪ fever ▪ bloody or black stool ▪ mucus in your stool

Stop use and ask a doctor if symptoms persist for more than 2 days or worsen.

PREGNANCY OR BREAST FEEDING

If pregnant or breast-feeding, ask a health professional before use.

Keep out of reach of children. In case of overdose, get medical help or contact a Poison Control Center right away.

DOSAGE AND ADMINISTRATION

Drink plenty of clear fluids to help prevent dehydration caused by diarrhea.

▪ Adults and children 6 years of age and older: At the onset of symptoms, dissolve 2 tablets in the mouth every 4 to 6 hours, up to 2 days maximum. Discontinue use as soon as symptoms disappear.

▪ Children under 6 years of age: Ask a doctor.

INACTIVE INGREDIENT

croscarmellose sodium, lactose, magnesium stearate

Questions or comments?

BoironUSA.com

Info@Boiron.com

1-800-BOIRON-1

(1-800-264-7661)

Other information ▪ do not use if glued carton end flaps are open or if the blister seal is broken ▪ store below 86°F (30°C)

DIARRHEA RELIEF*

Intestinal Pain ▪ Nausea ▪ Taveler's Diarrhea*

No Known Drug Interactions

60 Meltaway Tablets

Made in France

Distributed by Boiron Inc.

Newtown Square, PA 19073

*CLAIMS BASED ON TRADITIONAL HOMEOPATHIC PRACTICE, NOT ACCEPTED MEDICAL EVIDENCE. NOT FDA EVALUATED.
**C, K, CK, and X are homeopathic dilutions: see BoironUSA.com/info for details.